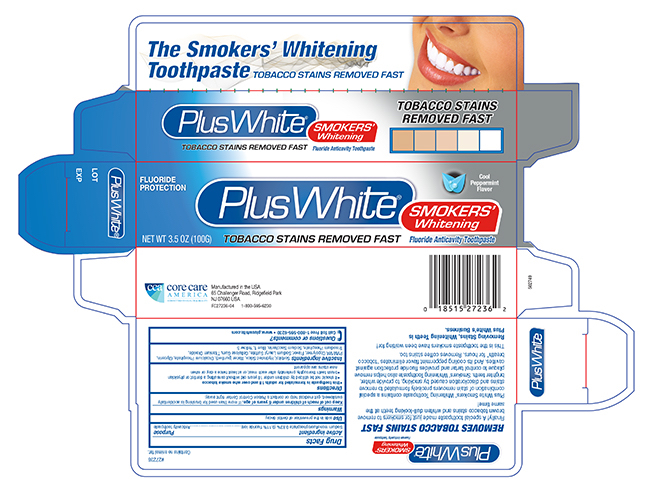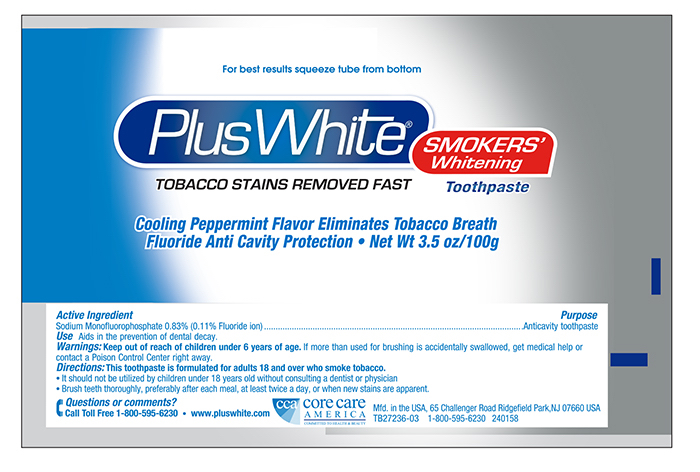 DRUG LABEL: Plus White Smokers Whitening
NDC: 61543-1554 | Form: PASTE, DENTIFRICE
Manufacturer: CCA Industries, Inc.
Category: otc | Type: HUMAN OTC DRUG LABEL
Date: 20191226

ACTIVE INGREDIENTS: SODIUM MONOFLUOROPHOSPHATE 0.83 g/100 g
INACTIVE INGREDIENTS: GLYCERIN; DIBASIC CALCIUM PHOSPHATE DIHYDRATE; WATER; HYDRATED SILICA; COPOVIDONE K25-31; TRISODIUM DIPHOSPHATE; SODIUM LAURYL SULFATE; CARBOXYMETHYLCELLULOSE SODIUM; TITANIUM DIOXIDE; SACCHARIN SODIUM

Plus White Smokers Whitening

Active Ingredient

Sodium Monofluorophosphate 0.83% (0.11% w/v fluoride ion)

Purpose

Anticavity Toothpaste

Uses

Aids in the prevention of dental decay.

Warnings

If more than used for brushing is accidentally swallowed, get medical help or contact a Poison Control Center right away.

Directions

This toothpaste is formulated for adults 18 and over who smoke tobacco

- It should not be utilized by children under 18 years old without consulting a dentist or physician
- Brush teeth thoroughly, preferably after each meal, or at least twice a day, or when new stains are apparent.

INACTIVE INGREDIENT

Inactive ingredients Sorbitol, Hydrated Silica, Water (Purified), Dicalcium Phosphate, Glycerin, PVM/MA Copolymer, Flavor, Sodium lauryl Sulfate, Cellulose Gum, Titanium Dioxide, Trisodium Phosphate, Sodium Saccharin, Blue 1, Yellow 5

Questions or comments? Call Toll Free1-800-595-6230
- www.pluswhite.com

Principal Display Panel -Tube 3.5 oz

Plus+White
THE SMOKER'S WHITENING TOOTHPASTE
Net Wt 3.5 oz (100G) - Fluoride Anticavity Toothpaste

Principal Display Panel - Carton 3.5 oz

Plus + White

The Smokers Whitening Toothpaste

NET WT 3.5 oz (100G) Fluoride Anticavity Toothpaste